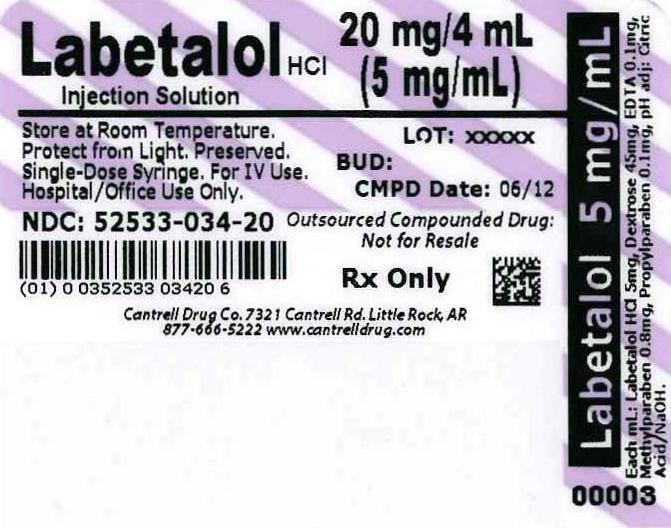 DRUG LABEL: Labetalol HCl
NDC: 52533-034 | Form: INJECTION, SOLUTION
Manufacturer: Cantrell Drug Company
Category: prescription | Type: HUMAN PRESCRIPTION DRUG LABEL
Date: 20140502

ACTIVE INGREDIENTS: LABETALOL HYDROCHLORIDE 5 mg/1 mL
INACTIVE INGREDIENTS: Water; Anhydrous Dextrose 45 mg/1 mL; Edetate Disodium 0.1 mg/1 mL; Methylparaben 0.8 mg/1 mL; Propylparaben 0.1 mg/1 mL; Citric Acid Monohydrate; Sodium Hydroxide

Labetalol HCl 5 mg/mL 4 mL Syringe